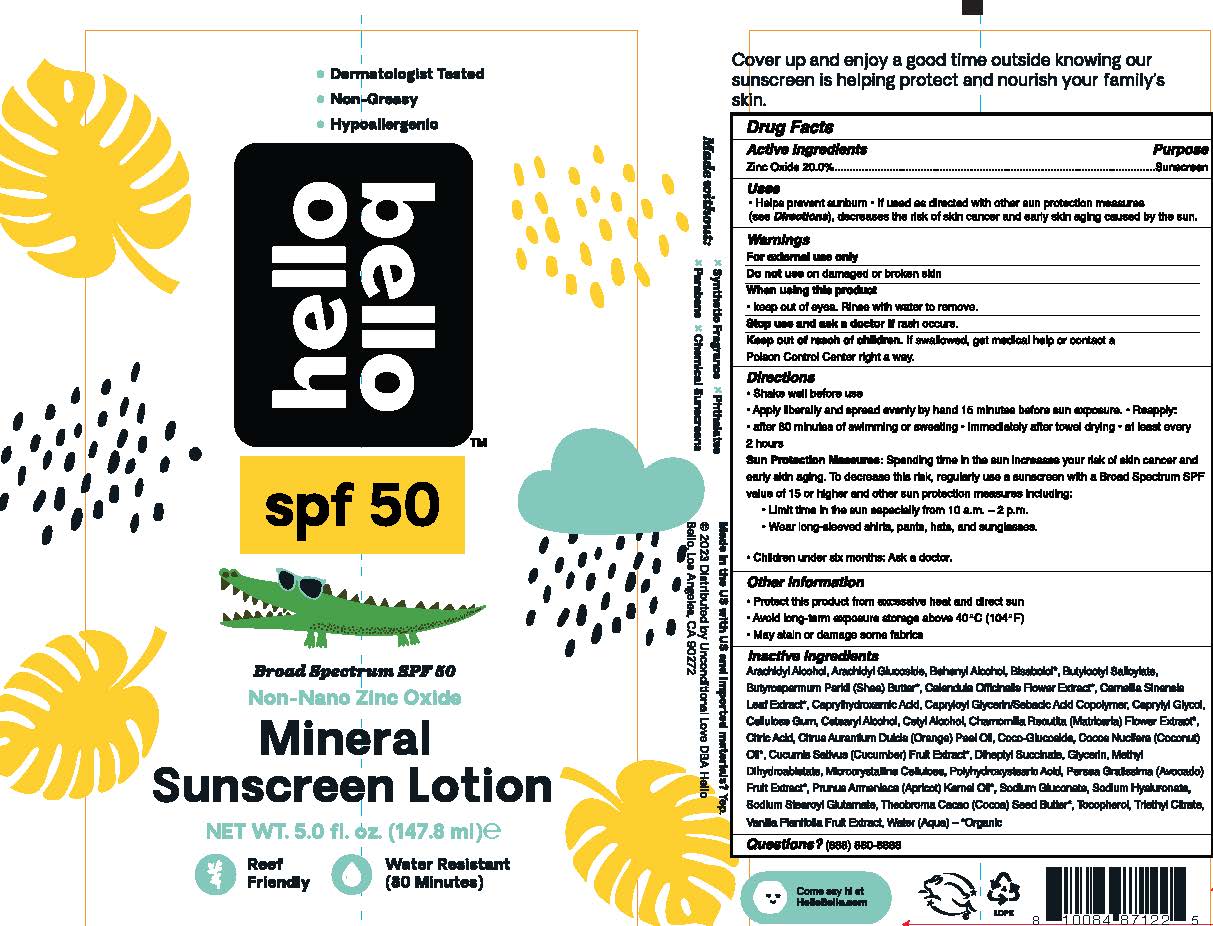 DRUG LABEL: Mineral Sunscreen SPF 50
NDC: 73418-102 | Form: LOTION
Manufacturer: Hello Bello
Category: otc | Type: HUMAN OTC DRUG LABEL
Date: 20250108

ACTIVE INGREDIENTS: ZINC OXIDE 200 mg/1 g
INACTIVE INGREDIENTS: ARACHIDYL ALCOHOL; ARACHIDYL GLUCOSIDE; DOCOSANOL; LEVOMENOL; BUTYLOCTYL SALICYLATE; SHEA BUTTER; CALENDULA OFFICINALIS FLOWER; GREEN TEA LEAF; CAPRYLHYDROXAMIC ACID; CAPRYLOYL GLYCERIN/SEBACIC ACID COPOLYMER (2000 MPA.S); CAPRYLYL GLYCOL; CARBOXYMETHYLCELLULOSE SODIUM; CETOSTEARYL ALCOHOL; CETYL ALCOHOL; CHAMOMILE; CITRIC ACID MONOHYDRATE; ORANGE OIL; COCO GLUCOSIDE; COCONUT OIL; CUCUMBER; DIHEPTYL SUCCINATE; GLYCERIN; METHYL DIHYDROABIETATE; MICROCRYSTALLINE CELLULOSE; AVOCADO; POLYHYDROXYSTEARIC ACID STEARATE; APRICOT KERNEL OIL; SODIUM GLUCONATE; HYALURONATE SODIUM; SODIUM STEAROYL GLUTAMATE; COCOA BUTTER; TOCOPHEROL; TRIETHYL CITRATE; VANILLA BEAN; WATER

Mineral Sunscreen Lotion SPF50

Active Ingredients

Zinc Oxide 20.0%

Purpose

Sunscreen

Uses

- Helps prevent sunburn
- If used as directed with other sun protection measures (see Directions), decreases the risk of skin cancer and early skin aging caused by the sun

Warnings

Do not use

on broken or damaged skin

When using this product

Keep out of eyes. Rinse with water to remove

Stop use and ask a doctor if

rash occurs

Keep out of reach of children.

If swallowed, get medical help or contact a Poison Control Center right away.

Directions

Shake well before use

Apply liberally and spread evenly by hand 15 minutes before sun exposure

Reapply:

- after 80 minutes of swimming or sweating immediately after towel use
- at least every 2 hours

Sun Protection Measures

Spending time in the sun can increase your risk of skin cancer and early skin aging. To decrease this risk, regularly use sunscreen with a Broad Spectrum SPF value of 15 or higher and other sun protection measures including:

- Limiting time in the sun, especially from 10a.m. - 2p.m.
- Wearing long-sleeved shirts, pants, hats and sunglasses

Children under six months: Ask a doctor

Other Information

Protect this product from excessive heat and direct sun

Avoid long-term exposure storage above 40°C (104°F)

May stain some fabrics

Inactive Ingredients

Arachidyl Alcohol, Arachidyl Glucoside, Behenyl Alcohol, Bisabolol*, Butyloctyl Salicylate, Butyrospermum Parkii (Shea) Butter*, Calendula Officinalis Flower Extract*, Camellia Sinensis (Green Tea) Leaf Extract*, Caprylhydroxamic Acid, Capryloyl Glycerin/Sebacic Acid Copolymer, Caprylyl Glycol, Cellulose Gum, Cetearyl Alcohol, Cetyl Alcohol, Chamomilla Recutita (Matricaria) Flower Extract*, Citric Acid, Citrus Aurantium Dulcis (Orange) Peel Oil, Coco Glucoside, Cocos Nucifera (Coconut) Oil*, Cucumis Sativus (Cucumber) Fruit Extract*, Diheptyl Succinate, Glycerin, Methyl Dihydroabietate, Microcrystalline Cellulose, Persea Gratissima (Avocado) Fruit Extract*, Polyhydroxystearic Acid, Prunus Armeniaca (Apricot) Kernel Oil*, Sodium Gluconate, Sodium Hyaluronate, Sodium Stearoyl Glutamate, Theobroma Cacao (Cocoa) Seed Butter, Tocopherol, Triethyl Citrate, Vanilla Planifolia Fruit Extract, Water (Aqua) *Organic

Questions?

(888)860-6888